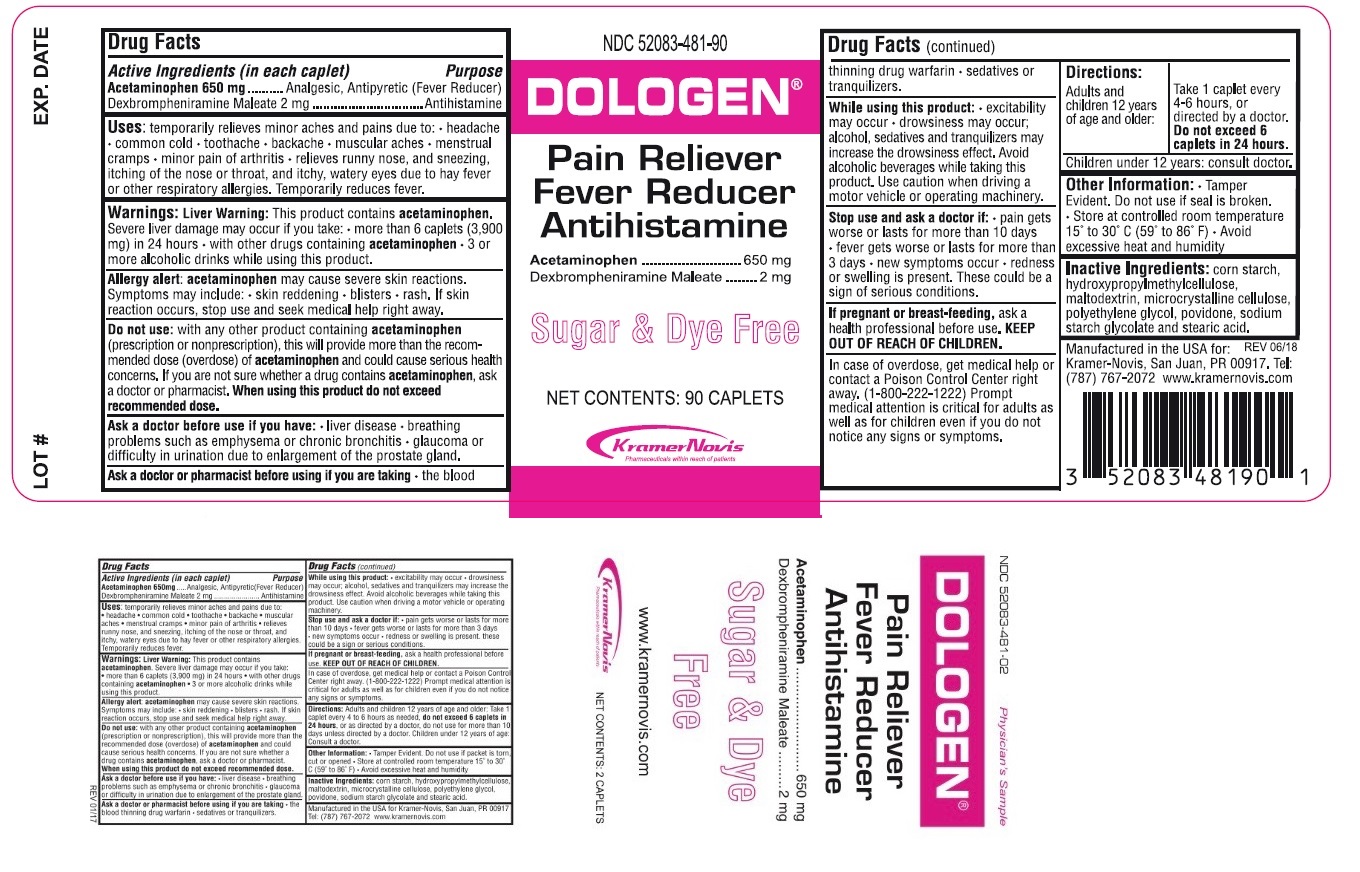 DRUG LABEL: Dologen
NDC: 52083-481 | Form: TABLET
Manufacturer: Kramer Novis
Category: otc | Type: HUMAN OTC DRUG LABEL
Date: 20181229

ACTIVE INGREDIENTS: DEXBROMPHENIRAMINE MALEATE 2 mg/1 1; ACETAMINOPHEN 650 mg/1 1
INACTIVE INGREDIENTS: STARCH, CORN; HYPROMELLOSE, UNSPECIFIED; MALTODEXTRIN; MICROCRYSTALLINE CELLULOSE; POLYETHYLENE GLYCOL, UNSPECIFIED; POVIDONE K30; SODIUM STARCH GLYCOLATE TYPE A POTATO; STEARIC ACID

Dologen

Active Ingredients (in each caplet)

Acetaminophen 650 mg

Dexbrompheniramine Maleate 2 mg

Purpose

Analgesic, Antipyretic (Fever Reducer)

Antihistamine

Uses:

temporarily relieves minor aches and pains due to: • headache • common cold • toothache • backache • muscular aches • menstrual cramps • minor pain of arthritis • relieves runny nose, and sneezing, itching of the nose or throat, and itchy watery eyes due to hay fever or other respiratory allergies. Temporarily reduces fever.

Warnings

Liver Warning: This product contains acetaminophen. Severe liver damage may occur if you take: • more than 6 caplets (3,900 mg) in 24 hours • with other drugs containing acetaminophen • 3 or more alcoholic drinks every day while using this product.

Allergy alert: acetaminophen may cause severe skin reactions. Symptoms may include: • skin reddening • blisters • rash. If skin reaction occurs, stop use and seek medical help right away.

Do not use : with any other product containing acetaminophen (prescription or nonprescription), this will provide more than the recommended dose (overdose) of acetaminophen and could cause serious health concerns If you are not sure whether a drug contains acetaminophen, ask a doctor or pharmacist. When using this product do not exceed recommended dose.

Ask a doctor before use if you have: •liver disease • breathing problems such as emphysema or chronic bronchitis • glaucoma or difficulty in urination due to enlargement of the prostate gland.

Ask a doctor or pharmacist before use if you are taking: • the blood thinning drug warfarin • sedatives or tranquilizers

While using this product:• excitability may occur • drowsiness may occur; alcohol, sedatives and tranquilizers may increase the drowsiness effect. Avoid alcoholic beverages while taking this product. Use caution when driving a motor vehicle or operating machinery.

Stop use and ask a doctor if: • pain gets worse or lasts for more than 10 days • fever gets worse or lasts more than 3 days • new symptoms occur • redness or swelling is present. These could be signs of a serious condition.

If pregnant or breast-feeding, ask a health professional before use.

KEEP OUT OF REACH OF CHILDREN

Overdose warning: In case of overdose, get medical help or contact a Poison Control Center right away (1-800-222-1222). Prompt medical attention is critical for adults as well as for children even if you do not notice any signs or symptoms.

Directions:

Adults and children 12 years of age and older: | take 1 caplet every 4 - 6 hours or as directed by a doctor; Do not exceed 6 caplets in 24 hours
Children under 12 years : Consult a doctor

Other Information:

• Tamper Evident. Do not use if seal is broken.

• Store at controlled room temperature 15° to 30°C (59° to 86°F). • Avoid excessive heat and humidity.

Inactive Ingredients:

corn starch, hydroxypropylmethylcellulose, maltodextrin, microcrystalline cellulose, polyethylene glycol, povidone, sodium starch glycolate and stearic acid

Pain Reliever

Fever Reducer

Antihistamine

Sugar & Dye Free

Manufactured in the USA for Kramer-Novis, San Juan, PR 00917. Tel: (787) 767-2072

www.kramernovis.com